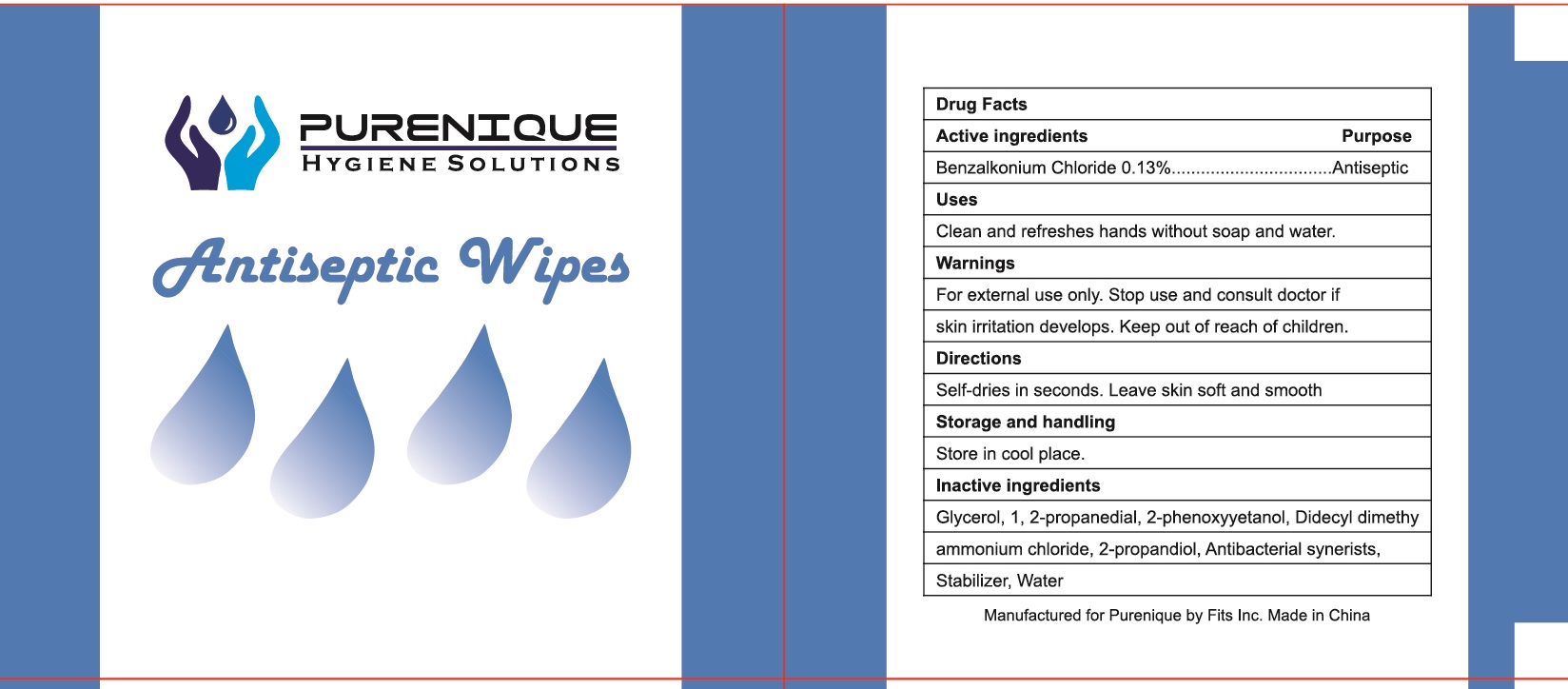 DRUG LABEL: Purenique Hygiene Solutions Antiseptic Wipes
NDC: 71734-331 | Form: SWAB
Manufacturer: JIANGMEN SHUIZIRUN SANITARY ARTICLES CO., LTD.
Category: otc | Type: HUMAN OTC DRUG LABEL
Date: 20201030

ACTIVE INGREDIENTS: benzalkonium chloride 0.13 g/100 g
INACTIVE INGREDIENTS: water; GLYCERIN; PROPYLENE GLYCOL

DRUG FACTS

Active Ingredient

Benzalkonium Chloride .......... 0.13 %

Purpose

Antiseptic

Uses:

Clean and refreshes hands without soap and water.

Warnings

DO NOT USE

For external use only. Stop use and consult doctor if skin irritation develops.

Keep out of reach of children.

if swallowed get medical help or contact a Poison Control Center right away.

Directions

Self-dries in seconds. Leave skin soft and smooth.

Other information:

Storage and handling: Store in cool place.

Inactive Ingredients:

Glycerol, 1,2-propanediol, 2-phenoxyetanol, Didecyl dimethyl ammonium chloride, 2-propandiol, Antibacterial synerists, Stabilizer, Water